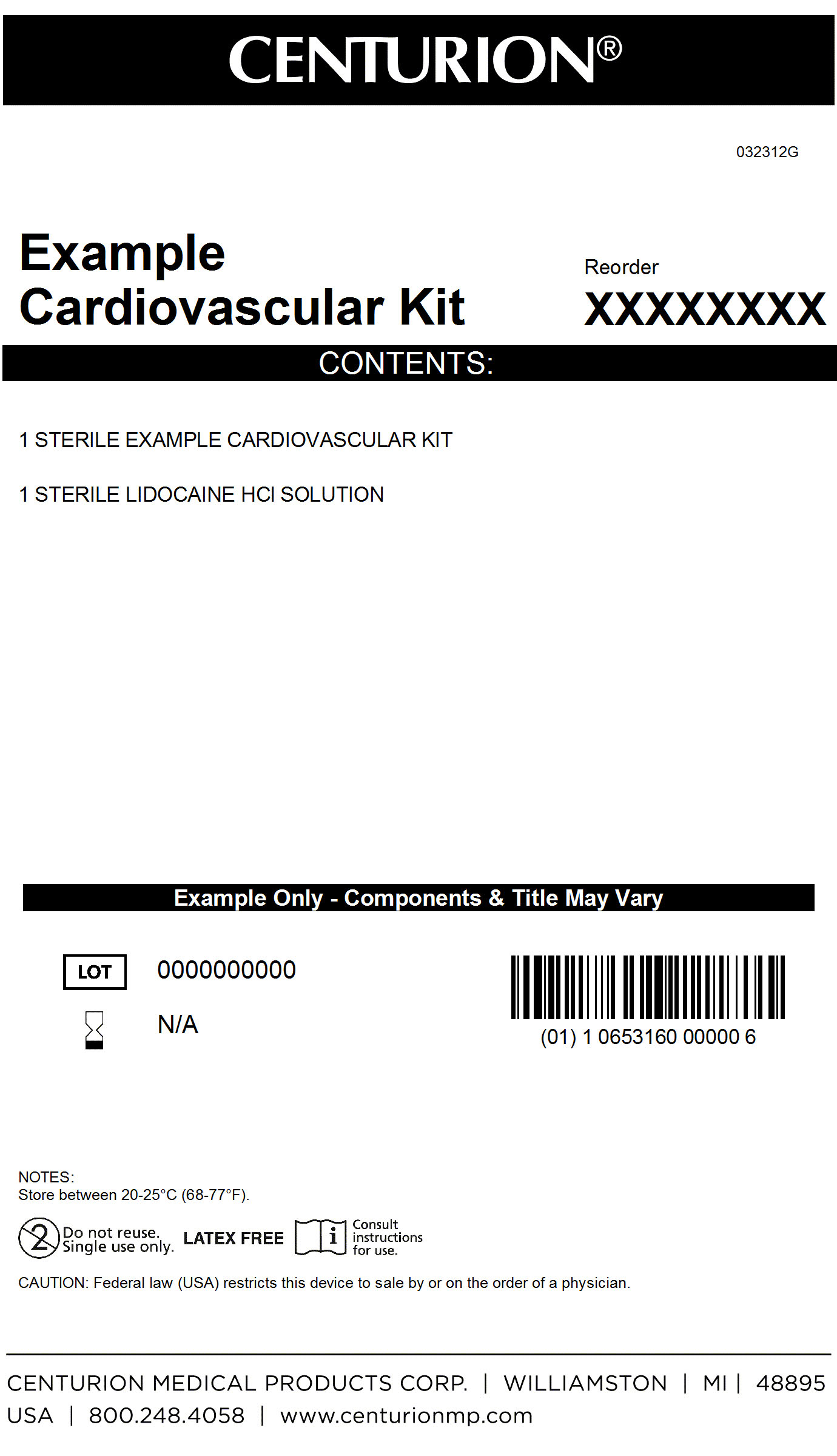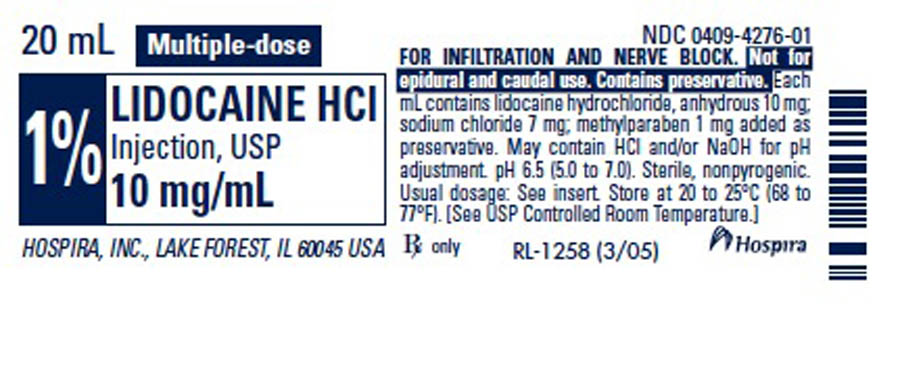 DRUG LABEL: Cardiovascular Procedure Kit
NDC: 24840-1108 | Form: KIT | Route: INFILTRATION
Manufacturer: Centurion Medical Products
Category: other | Type: MEDICAL DEVICE
Date: 20120809

ACTIVE INGREDIENTS: LIDOCAINE HYDROCHLORIDE ANHYDROUS 10 mg/1 mL
INACTIVE INGREDIENTS: SODIUM CHLORIDE 7 mg/1 mL; WATER; SODIUM HYDROXIDE; HYDROCHLORIC ACID; METHYLPARABEN 1 mg/1 mL

Cardiovascular Procedure Kit

DESCRIPTION

Lidocaine Hydrochloride Injection, USP is a sterile, nonpyrogenic solution of lidocaine hydrochloride in water for injection for parenteral administration in various concentrations. Multiple-dose vials contain 0.1% of methylparaben added as preservative. May contain sodium hydroxide and/or hydrochloric acid for pH adjustment. The pH is 6.5 (5.0 to 7.0). Lidocaine is a local anesthetic of the amide type. Lidocaine Hydrochloride, USP is a white powder freely soluable in water. The molecular weight is 288.82. The semi-rigid vial used for the plastic vials is fabricated from a specially formulated polyolefin. It is a copolymer of ethylene and propylene.